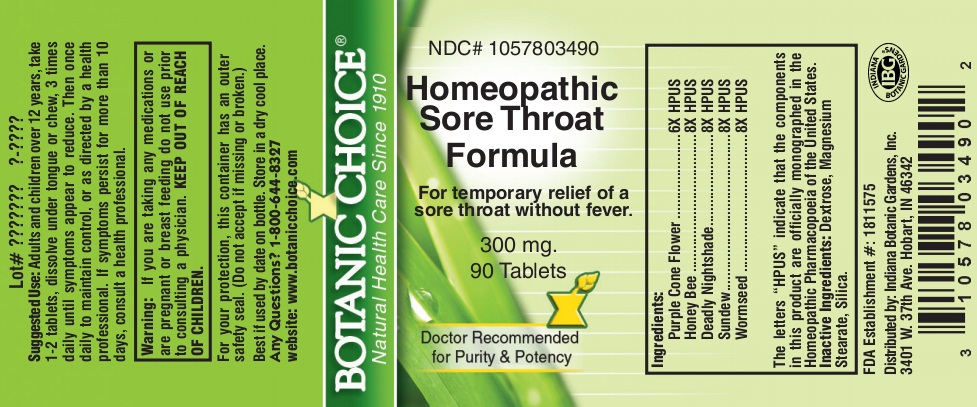 DRUG LABEL: Homeopathic Sore Throat Formula
NDC: 10578-034 | Form: TABLET
Manufacturer: Indiana Botanic Gardens
Category: homeopathic | Type: HUMAN OTC DRUG LABEL
Date: 20140401

ACTIVE INGREDIENTS: ECHINACEA ANGUSTIFOLIA 6 [hp_X]/1 1; APIS MELLIFERA 8 [hp_X]/1 1; ATROPA BELLADONNA 8 [hp_X]/1 1; DROSERA ROTUNDIFOLIA 8 [hp_X]/1 1; ARTEMISIA CINA PRE-FLOWERING TOP 8 [hp_X]/1 1
INACTIVE INGREDIENTS: DEXTROSE; MAGNESIUM STEARATE; SILICON DIOXIDE

Homeopathic Sore Throat Formula

Suggested Use:

Adults and children over 12 years, take 1-2 tablets, dissolve under tongue or chew, 3 times daily until symptoms appear to reduce. Then once daily to maintain control, or as directed by a health professional.

STOP USE

If symptoms persist for more than 10 days, consult a health professional.

Warning:

If you are taking any medications or are pregnant or breast feeding do not use prior to consulting a physician.

KEEP OUT OF REACH OF CHILDREN.

For your protection, this container has an outer safety seal. (Do not accept if missing or broken.)

Best if used by date on bottle. Store in a dry cool place.

Any Questions? 1-800-644-8327

website: www.botanicchoice.com

INDICATIONS AND USAGE

For temporary relief of a sore throat without fever.

PURPOSE

For temporary relief of a sore throat without fever.

Ingredients:

Purple Cone Flower ......................6X HPUS

Honey Bee ................................8X HPUS

Deadly Nightshade .......................8X HPUS

Sundew ....................................8X HPUS

Wormseed .................................8X HPUS

The letters "HPUS" indicate that the components in this product are officially monographed in the Homeopathic Pharmacopoeia of the United States.

Inactive Ingredients:

Dextrose, Magnesium Stearate, Silica.

FDA Establishment #: 1811575

Distributed by: Indiana Botanic Gardens, Inc.

3401 W. 37th Ave. Hobart, IN 46342

Botanic Choice

Natural Health Care Since 1910

NDC# 1057803490

Homeopathic Sore Throat Formula

For temporary relief of a sore throat without fever.

300 mg.

90 Tablets